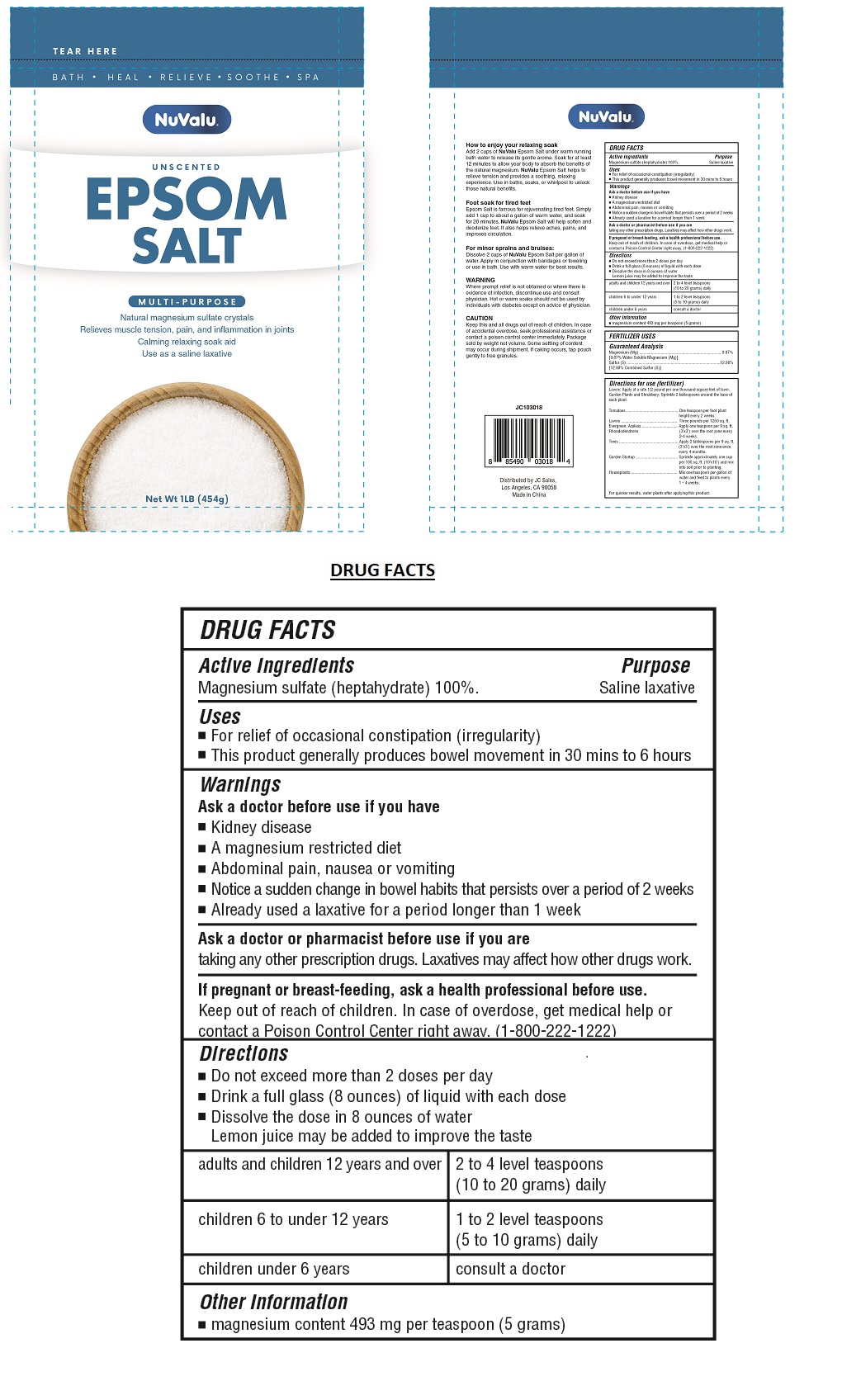 DRUG LABEL: NuValu Epsom Salt
NDC: 72520-002 | Form: GRANULE
Manufacturer: J C SALES
Category: otc | Type: HUMAN OTC DRUG LABEL
Date: 20241204

ACTIVE INGREDIENTS: MAGNESIUM SULFATE HEPTAHYDRATE 100 g/100 g

NuValu Epsom Salt

Active Ingredients

Magnesium sulfate (heptahydrate) 100%

Purpose

Saline laxative

Uses

- For relief of occasional constipation (irregularity)
- This product generally produces bowel movement in 30 mins to 6 hours

Warnings

Ask a doctor before use if you have

• Kidney disease

• A magnesium restricted diet

• Abdominal pain, nausea or vomiting

• Notice a sudden change in bowel habits that persists over a period of 2 weeks

• Already used a laxative for a period longer than 1 week

Ask a doctor or pharmacist before use if you are

taking any other prescription drugs. Laxatives may affect how other drugs work

If pregnant or breast-feeding, ask a health professional before use.

Keep out of reach of children. In case of overdose, get medical help or contact a Poison Control Center right away. (1-800-222-1222)

Directions

- Do not exceed more than 2 doses per day
- Drink a full glass (8 ounces) of liquid with each dose
- Dissolve the dose in 8 ounces of water.
  Lemon juice may be added to improve the taste.

adults and children 12 years and over | 2 to 4 level teaspoons (10 to 20 grams) daily
children 6 to under 12 years | 1 to 2 level teaspoons (5 to 10 grams) daily
children under 6 years | consult a doctor

Other Information

- magnesium content 493 mg per teaspoon (5 grams)

Inactive Ingredients

none

UNSCENTED

MULTI-PURPOSE

Natural magnesium sulfate crystals

Use as a saline laxative

Package sold by weight not volume. Some settling of content may occur during shipment. If caking occurs, tap pouch gently to free granules.

Distributed by JC Sales,

Los Angeles, CA 90058

Made in China